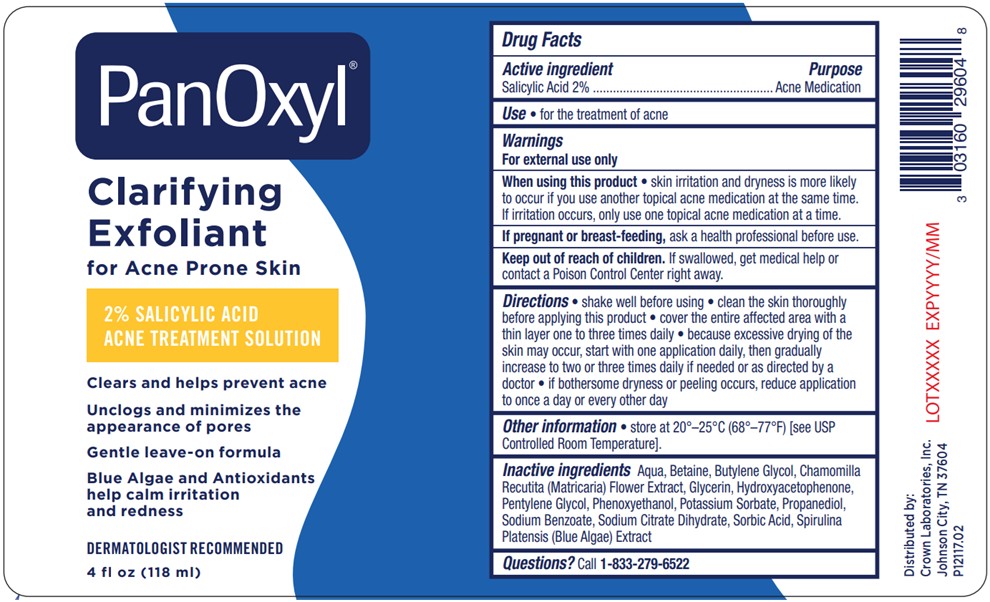 DRUG LABEL: PanOxyl Clarifying Exfoliant
NDC: 0316-0296 | Form: LIQUID
Manufacturer: Crown Laboratories, Inc.
Category: otc | Type: HUMAN OTC DRUG LABEL
Date: 20260112

ACTIVE INGREDIENTS: SALICYLIC ACID 2 g/100 mL
INACTIVE INGREDIENTS: BETAINE; BUTYLENE GLYCOL; MATRICARIA CHAMOMILLA FLOWERING TOP; GLYCERIN; HYDROXYACETOPHENONE; PENTYLENE GLYCOL; PHENOXYETHANOL; POTASSIUM SORBATE; PROPANEDIOL; WATER; SODIUM BENZOATE; SORBIC ACID; TRISODIUM CITRATE DIHYDRATE; SPIRULINA PLATENSIS

PanOxyl Clarifying Exfoliant

Active ingredient

Salicylic Acid 2%

Purpose

Acne Medication

Use

- for the treatment of acne

Warnings

For external use only

When using this product

- skin irritation and dryness is more likely to occur if you use another topical acne medication at the same time. If irritation occurs, only use one topical acne medication at a time

If pregnant or breast-feeding,

ask a health professional before use.

Keep out of reach of children.

If swallowed, get medical help or contact a Poison Control Center right away.

Directions

- shake well before using
- clean the skin thoroughly before applying this product
- cover the entire affected area with a thin layer one to three times daily
- because excessive drying of the skin may occur, start with one application daily, then gradually increase to two or three times daily if needed or as directed by a doctor
- if bothersome dryness or peeling occurs, reduce application to once a day or every other day

Other information

- Store at 20o - 25oC (68o - 77oF) [see USP Controlled Room Temperature].

Inactive ingredients

Betaine, Butylene Glycol, Chamomilla Recutita (Matricaria) Flower Extract, Glycerin, Hydroxyacetophenone, Pentylene Glycol, Phenoxyethanol, Potassium Sorbate, Propanediol, Purified Water, Sodium Benzoate, Sodium Citrate Dihydrate, Sorbic Acid, Spirulina Platensis (Blue Algae) Extract

Questions?

call 1-833-279-6522

Panoxyl Clarifying Exfoliant Bottle

PanOxyl®

Clarifying Exfoliant

for Acne Prone Skin

2% SALICYLIC ACID

ACNE TREATMENT SOLUTION

Clears and helps prevent acne

Unclogs and minimizes the appearance of pores

Gentle leave-on formula

Blue Algae and Antioxidants help calm irritation and redness

DERMATOLOGIST RECOMMENDED

4 fl oz (118 mL)

P12117.02